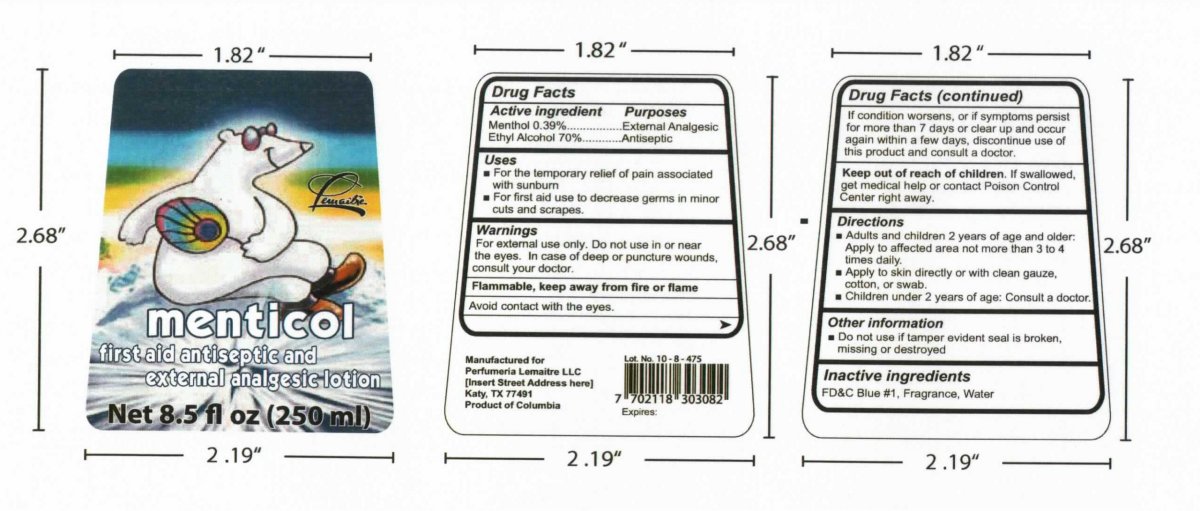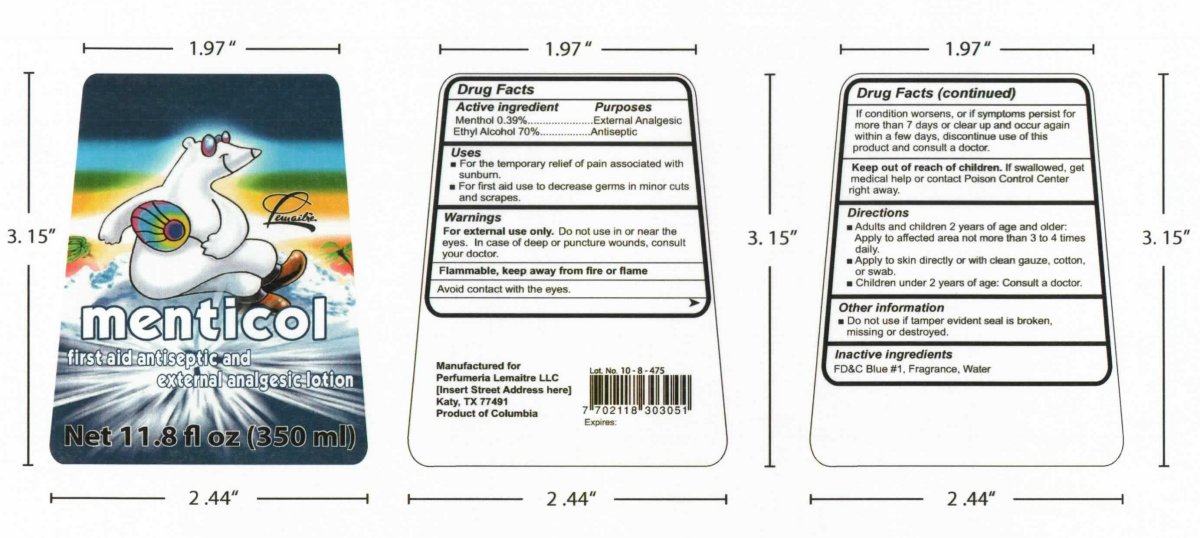 DRUG LABEL: Menticol first aid antiseptic and external analgesic lotion
NDC: 49199-100 | Form: LOTION
Manufacturer: Perfumeria Lemaitre S.A.
Category: otc | Type: HUMAN OTC DRUG LABEL
Date: 20091102

ACTIVE INGREDIENTS: ALCOHOL 0.39 mL/100 mL; MENTHOL 70 mL/100 mL
INACTIVE INGREDIENTS: FD&C BLUE NO. 1; WATER

Menticol first aid antiseptic and external analgesic lotion

Drug Facts

Active Ingredient Purposes

Menthol 0.39 percent External Analgesic

Ethyl Alcohol 70 percent Antiseptic

Uses

For the temporary relief of pain associated with sunburn

For first aid use to decrease germs in minor cuts and scrapes

Warnings

For external use only.

Do not use in or near the eyes.

In case of deep or puncture wounds, consult your doctor.

STORAGE AND HANDLING

Flammable, keep away from fire or flame

WARNINGS AND PRECAUTIONS

Avoid contact with the eyes.

If condition worsens, or if symptoms persist for more than 7 days or clear up and occur again within a few days, discontinue use of this product and consult a doctor.

Keep out of reach of children.

If swallowed, get medical help or contact Poison Control Center right away.

Directions

Adults and children 2 years of age and older: Apply to affected area not more than 3 to 4 times daily.

Apply to skin directly or with clean gauze, cotton or swab.

Children under 2 years of age: Consult a doctor.

Other information

Do not use if tamper evident seal is broken, missing or destroyed

INACTIVE INGREDIENT

FD C Blue #1, Fragrance, Water

DESCRIPTION

Manufactured for

Perfumeria Lemaitre LLC

Katy, TX 77491
Product of Columbia

PACKAGE LABEL

menticol

first aid antiseptic and external analgesic lotion

Net 8.5 fl oz 250 ml

PACKAGE LABEL

menticol

first aid antiseptic and external analgesic lotion

Net 11.8 fl oz 350 ml

PACKAGE LABEL

Enter section text here